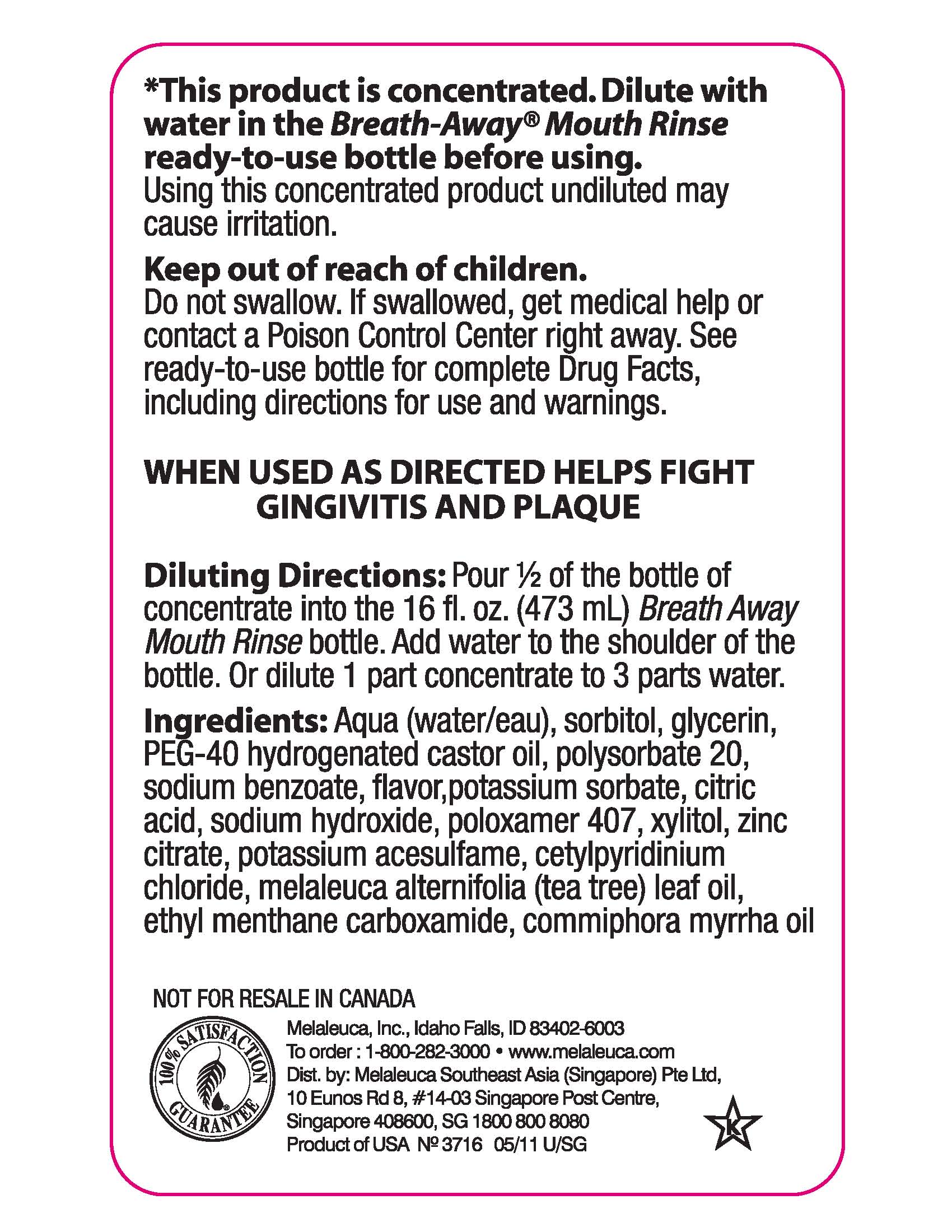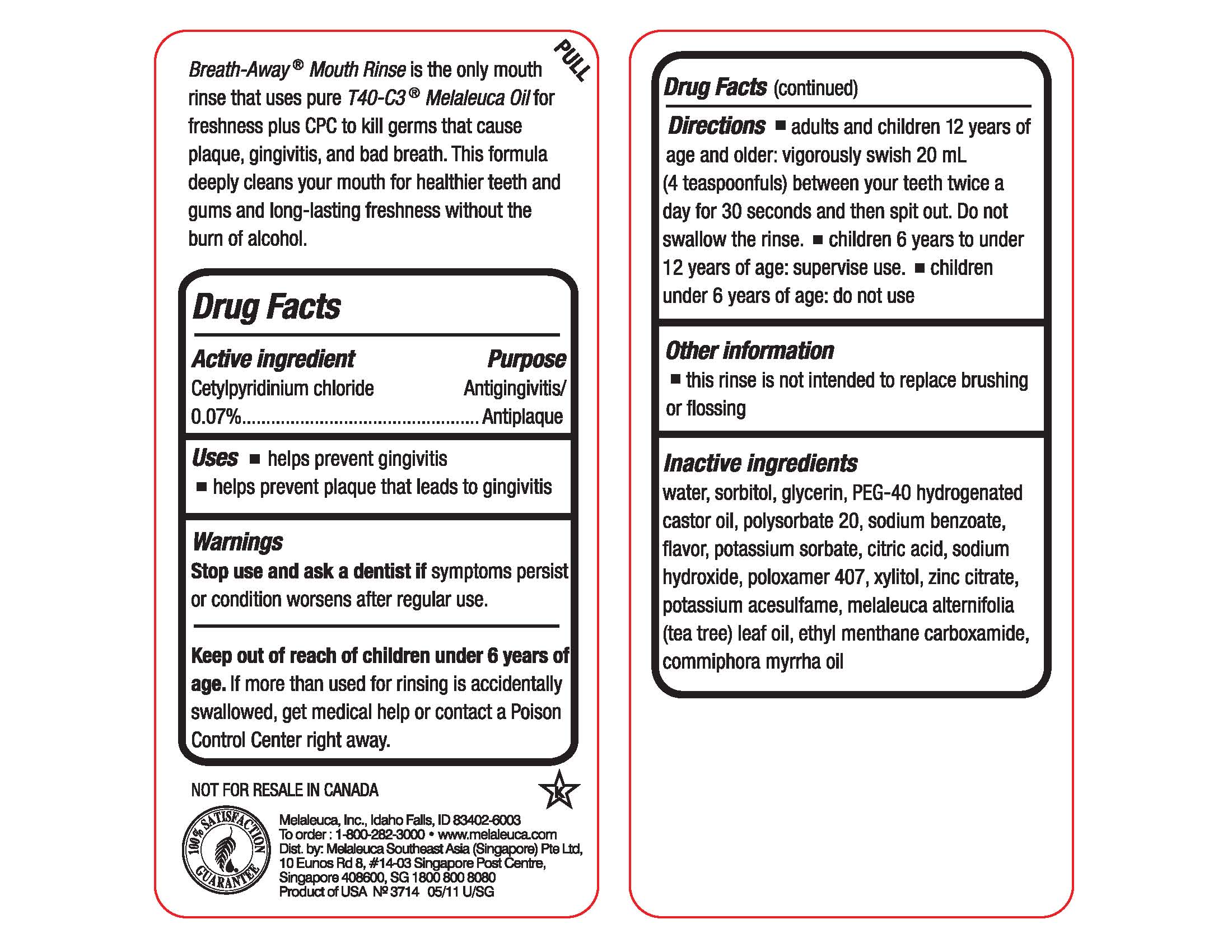 DRUG LABEL: BreathAway
NDC: 54473-294 | Form: MOUTHWASH
Manufacturer: Melaleuca, Inc.
Category: otc | Type: HUMAN OTC DRUG LABEL
Date: 20230130

ACTIVE INGREDIENTS: CETYLPYRIDINIUM CHLORIDE 0.3394 g/473 mL
INACTIVE INGREDIENTS: ACESULFAME POTASSIUM; ANHYDROUS CITRIC ACID; ETHYL MENTHANE CARBOXAMIDE; GLYCERIN; MYRRH OIL; POLOXAMER 407; POLYOXYL 40 HYDROGENATED CASTOR OIL; POLYSORBATE 20; POTASSIUM SORBATE; SODIUM BENZOATE; SODIUM HYDROXIDE; SORBITOL; TEA TREE OIL; WATER; XYLITOL; ZINC CITRATE

BreathAway Mouth Rinse Fresh Mint

Active ingredient
Cetylpyridinium chloride 0.07%

Purpose
Antigingivitis/Antiplaque

Uses

- helps prevent gingivitis
- helps prevent plaque that leads to gingivitis

Warnings
Stop use and ask a dentist if symptoms persist or condition worsens after regular use.

Keep out of reach of children under 6 years of age. If more than used for rinsing is accidentally swallowed, get medical help or contact a Poison Control Center right away.

Directions

- adults and children 12 years of age and older: vigorously swish 20 mL (4 teaspoonfuls) between your teeth twice a day for 30 seconds and then spit out. Do not swallow the rinse.
- children 6 years to under 12 years of age: supervise use.
- children under 6 years of age: do not use

Inactive ingredients
water, sorbitol, glycerin, PEG-40 hydrogenated castor oil, polysorbate 20, sodium benzoate, flavor, potassium sorbate, citric acid, sodium hydroxide, poloxamer 407, xylitol, zinc citrate, potassium acesulfame, melaleuca alternifolia (tea tree) leaf oil, ethyl menthane carboxamide, commiphora myrrha oil